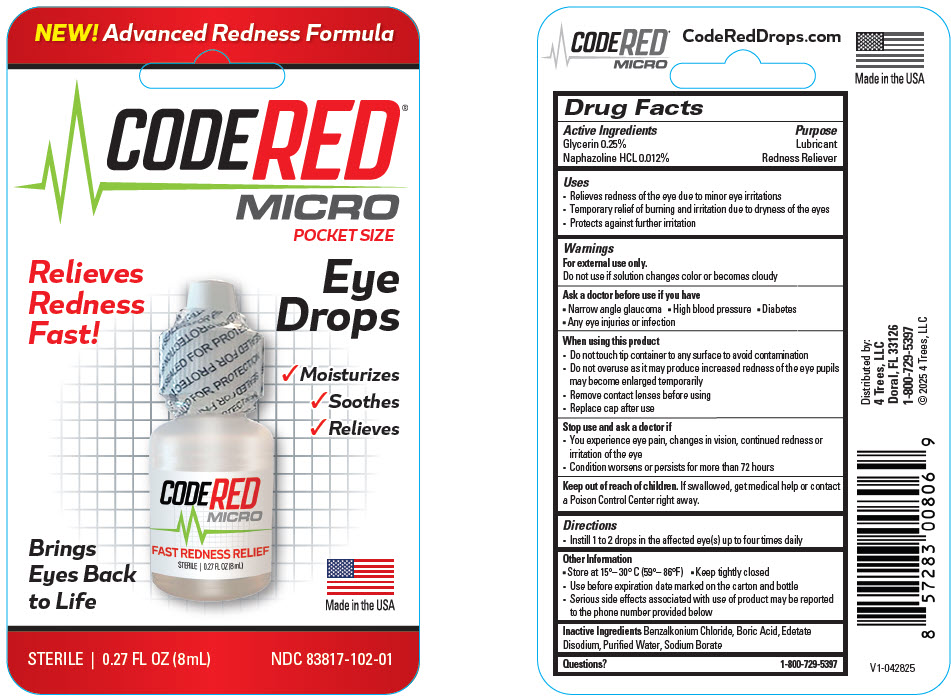 DRUG LABEL: Code Red Eye Drops
NDC: 83817-102 | Form: SOLUTION/ DROPS
Manufacturer: 4 Trees LLC
Category: otc | Type: HUMAN OTC DRUG LABEL
Date: 20250529

ACTIVE INGREDIENTS: GLYCERIN 20 mg/8 mL; NAPHAZOLINE HYDROCHLORIDE 0.96 mg/8 mL
INACTIVE INGREDIENTS: BENZALKONIUM CHLORIDE; BORIC ACID; EDETATE DISODIUM; WATER; SODIUM BORATE

Code Red Eye Drops
Micro

Drug Facts

ACTIVE INGREDIENT

Active Ingredients | Purpose
Glycerin 0.25% | Lubricant
Naphazoline HCL 0.012% | Redness reliever

Uses

- relieves redness of the eye due to minor eye irritations
- temporary relief of burning and irritation due to dryness of the eyes
- protects against further irritation

Warnings

For external use only.

Do not use if solution changes color or becomes cloudy

Ask a doctor before use if you have

- narrow angle glaucoma
- high blood pressure
- diabetes
- any eye injuries or infection

When using this product

- do not touch tip of container to any surface to avoid contamination
- do not use if this solution changes color or becomes cloudy
- pupils may become enlarged temporarily
- remove contact lenses before using
- replace cap after each use

Stop use and ask a doctor if

- you feel eye pain
- changes in vision, continued redness or irritation of the eye
- condition worsens or persists for more than 72 hours

Keep out of reach of children.

If swallowed, get medical help or contact a Poison Control Center right away.

Directions

- Instill 1 to 2 drops in the affected eye(s) up to four times daily

Other information

- store at 15°–30°C (59°–86°F)
- keep tightly closed
- use before expiration date marked on the carton and bottle
- serious side effects associated with use of product may be reported to the phone number provided below

Inactive ingredients

Benzalkonium Chloride, Boric Acid, Edetate Disodium, Purified Water, Sodium Borate

Questions?

1-888-995-9935

Manufactured by:
Samson®
Pharmaceuticals Inc.

PRINCIPAL DISPLAY PANEL - 8 mL Bottle Blister Pack

NEW! Advanced Redness Formula

CODE RED®
MICRO

POCKET SIZE

Relieves
Redness
Fast!

Eye
Drops

✓ Moisturizes
✓ Soothes
✓ Relieves

Brings
Eyes Back
to Life

Made in the USA

STERILE | 0.27 FL OZ (8 mL)
NDC 83817-102-01